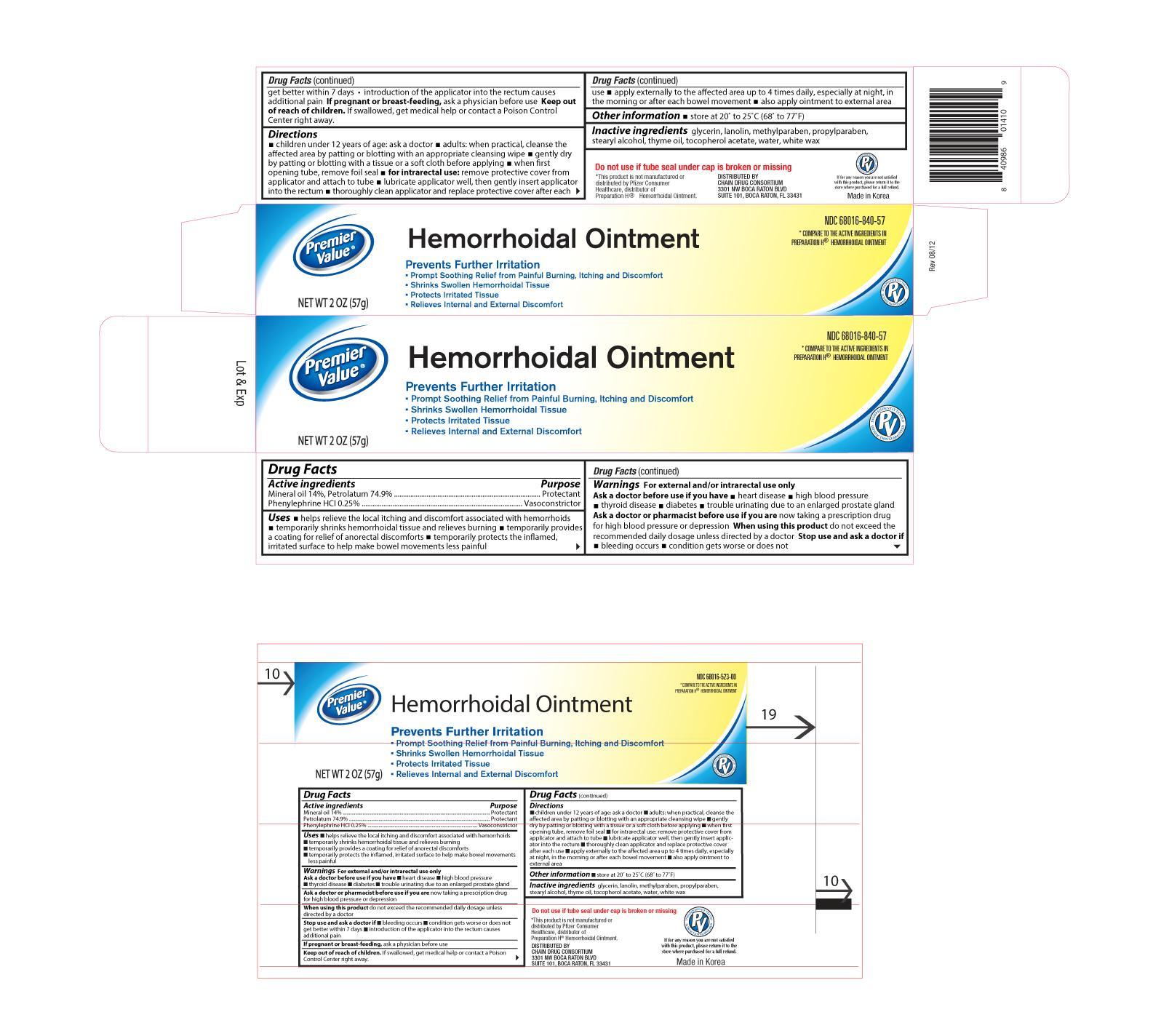 DRUG LABEL: Premier Value Hemorrhoidal
NDC: 68016-840 | Form: OINTMENT
Manufacturer: Chain Drug Consortium, LLC
Category: otc | Type: HUMAN OTC DRUG LABEL
Date: 20150211

ACTIVE INGREDIENTS: MINERAL OIL 140 mg/1 g; PETROLATUM 749 mg/1 g; PHENYLEPHRINE HYDROCHLORIDE 2.5 mg/1 g
INACTIVE INGREDIENTS: GLYCERIN; LANOLIN; METHYLPARABEN; PROPYLPARABEN; STEARYL ALCOHOL; THYME OIL; WATER; WHITE WAX

Active ingredients Purpose

Mineral Oil 14%................................................................ Protectant

Petrolatum 74.9%............................................................. Protectant

Phenylephrine HCI 0.25%................................................... Vasconstrictor

Uses

- helps relieve the local itching and discomfort associated with hemorrhoids
- temporarily shrinks hemorrhoidal tissue and relieves burning
- temporarily provides a coating for relief of anorectal discomforts
- temporarily protects the inflamed, irritated surface to help make bowel movements less painful

Warnings

For external and/or intrarectal use only

Ask a doctor or pharmacist before use if you are now taking a prescription drug for high blood pressure or depression

When using this product do not exceed the recommended daily dosage unless directed by a doctor

Stop use and ask a doctor if

- bleeding occurs
- condition gets worse or does not get better within 7 days
- introduction of the applicator into the rectum causes additional pain

PREGNANCY OR BREAST FEEDING

If pregnant or breast-feeding, ask a physician before use

Keep out of reach of children. If swallowed, get medical help or contact a Poison Control Center right away.

Directions

- children under 12 years of age: ask a doctor
- adults: when practical, cleanse the affected area by patting or blotting with an appropriate cleansing wipe
- gently dry by patting or blotting with a tissue or soft cloth before applying
- when first opening tube, remove foil seal
- for intrarectal use: remove protective cover from applicator and attach to tube
- lubricate well, then gently insert applicator into the rectum
- thoroughly clean applicator and replace protective cover after each use
- apply externally to the affected area up to 4 times daily, especially at night, in the morning, or after each bowel movement
- also apply to external area

Other information

- store at 20° to 25°C (68° to 77°F)

Inactive ingredients

glycerin, lanolin, methylparaben, propylparaben, stearyl alcohol, thyme oil, tocopherol acetate, water, white wax

DOSAGE AND ADMINISTRATION

DISTRIBUTED BY:

CHAIN DRUG CONSORTIUM

3301 NW BOCA RATON BLVD

SUITE 101

BOCA RATON, FL 33431

MADE IN KOREA